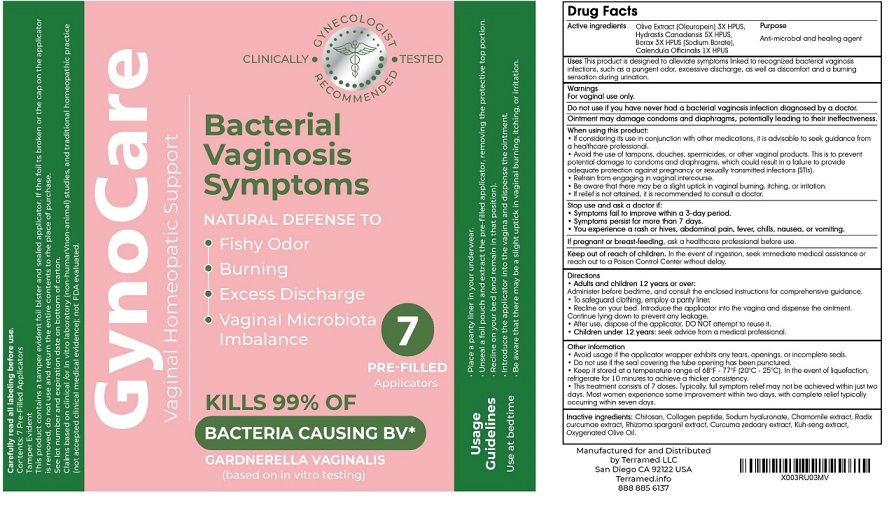 DRUG LABEL: Terramed Just Think Comfort gyno care
NDC: 83004-005 | Form: GEL
Manufacturer: Rida LLC
Category: homeopathic | Type: HUMAN OTC DRUG LABEL
Date: 20250310

ACTIVE INGREDIENTS: OLEUROPEIN 3 [hp_X]/100 mL; GOLDENSEAL 5 [hp_X]/100 mL; SODIUM BORATE 3 [hp_X]/100 mL; CALENDULA OFFICINALIS FLOWERING TOP 1 [hp_X]/100 mL
INACTIVE INGREDIENTS: POLIGLUSAM; POVIDONE-IODINE; SODIUM; CHAMAEMELUM NOBILE FLOWER; CURCUMA KWANGSIENSIS ROOT; SPARGANIUM STOLONIFERUM ROOT; CURCUMA ZEDOARIA WHOLE; OLIVE OIL

Drug Facts

Active Ingredient

Olive Extract (oleuropein) 3X HPUS
Hydrastis Canadensis 5X HPUS
Borax (Sodium Borate) 3X HPUS
Calendula Officinalis 1X HPUS

Purpose

Anti-microbial and Healing agent

Uses

This product is designed to alleviate symptoms linked to recognized bacterial vaginosis infecfions, such as a pungent odor, excessive discharge, as well as discomfort and a burning sensation during urination.

Warnings

- For vaginal use only.
- Do not use if you have never had bacterial vaginosis infection diagnosed by a doctor.
- Ointment may damage condoms and diaphragms, potentially leading to their Ineffectiveness.

When using this product:

- If considering its use in conjunction with other medications, it is advisable to seek guidance from a healthcare professional.
- Avoid the use of tampons, douches, spermicides, or other vaginal products. This is to prevent potential damage to condoms and diaphragms, which could result in a failure to provide adequate protection against pregnancy or sexually transmitted infections (STIs).
- Refrain from engaging in vaginal intercourse
- Be aware that there may be a slight uptick in vaginal burning, itching, or irritation
- If relief is not attained, it is recommended to consult a doctor.

Stop use and ask a doctor if

- symptoms do not get better in 3 days
- symptoms persist for more than 7 days
- You experience a rash or hives, abdominal pain, fever, chills, nausea, or vomiting.

If pregnant or breast-feedingask a healthcare professional before use.

Keep out of the reach of childrenIf swallowed, get medical help or contact Poison Control Center right away

Directions

Adults and children 12 years or over

Administer before bedtime, and consult the enclosed instructions for comprehensive guidance.

- To safeguard clothing. employ a panty liner.
- Recline on your bed. introduce the applicator into the vagina and dispense the ointment.Continue lying down to prevent any leakage.
- After use, dispose of the applicator. DO NOT attempt to reuse it.
- Children under 12 years: seek advice from a medical professional.

Other information

- Avoid usage if the applicator wrapper exhibits any tears, openings, or incomplete seals.
- Do not use if the seal covering the tube opening has been punctured.
- Keep it stored at a temperature range of 68°F - 77°F {20°C - 25°C]. In the event of liquefaction, refrigerate for 10 minutes to achieve a thicker consistency
- This treatment consists of 7 doses. Typically, full symptom relief may not be achieved within just two days. Most women experience some improvement within two days. with complete relief typically occurring within seven days.

Inactive Ingredients

Chitosan, povidone-iodine, Sodum hyaluronate, Chamomile extract, Radix curcumae extract, Rhizome sparganil extract, Curcuma zedoary extract, Kuh-seng extract, Oxygenated Olive Oil